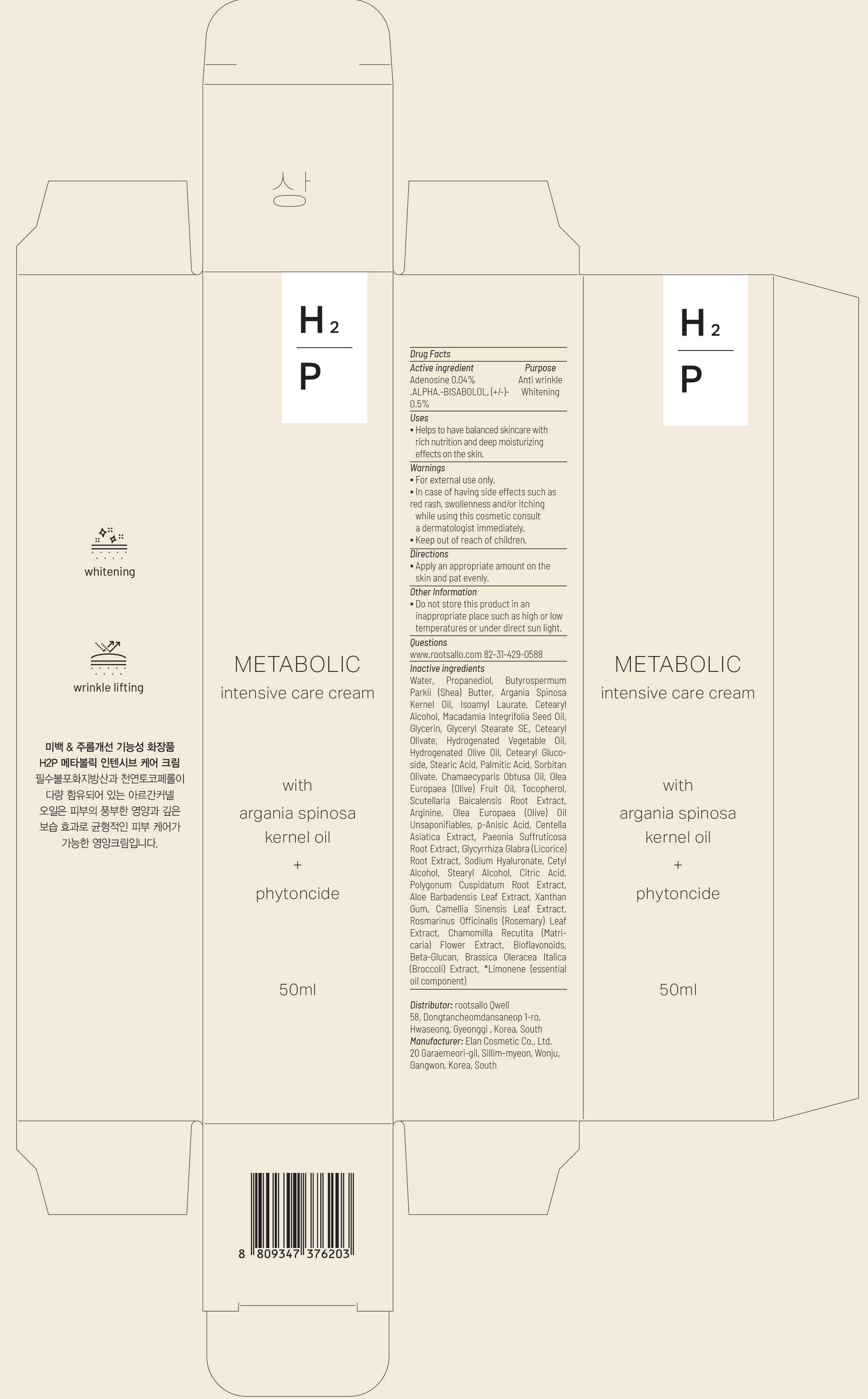 DRUG LABEL: METABOLIC INTENSIVE CARE
NDC: 82450-020 | Form: CREAM
Manufacturer: rootsallo Qwell
Category: otc | Type: HUMAN OTC DRUG LABEL
Date: 20211230

ACTIVE INGREDIENTS: Adenosine 0.04 g/100 mL; .ALPHA.-BISABOLOL, (+/-)- 0.5 g/100 mL
INACTIVE INGREDIENTS: Water; Propanediol; SHEA BUTTER

ACTIVE INGREDIENTS

Adenosine 0.04%
.ALPHA.-BISABOLOL, (+/-)- 0.5%

PURPOSE

Anti wrinkle, Whitening

Uses

Helps to have balanced skincare with rich nutrition and deep moisturizing effects on the skin.

Warnings

For external use only.
In case of having side effects such as red rash, swollenness and/or itching while using this cosmetic consult a dermatologist immediately.
Keep out of reach of children.

KEEP OUT OF REACH OF CHILDREN

Directions

Apply an appropriate amount on the skin and pat evenly.

Other Information

Do not store this product in an inappropriate place such as high or low temperatures or under direct sun light.

Questions

www.rootsallo.com 82-31-429-0588

Inactive ingredients

Water, Propanediol, Butyrospermum Parkii (Shea) Butter, Argania Spinosa Kernel Oil, Isoamyl Laurate, Cetearyl Alcohol, Macadamia Integrifolia Seed Oil, Glycerin, Glyceryl Stearate SE, Cetearyl Olivate, Hydrogenated Vegetable Oil, Hydrogenated Olive Oil, Cetearyl Glucoside, Stearic Acid, Palmitic Acid, Sorbitan Olivate, Chamaecyparis Obtusa Oil, Olea Europaea (Olive) Fruit Oil, Tocopherol, Scutellaria Baicalensis Root Extract, Arginine, Olea Europaea (Olive) Oil Unsaponifiables, p-Anisic Acid, Centella Asiatica Extract, Paeonia Suffruticosa Root Extract, Glycyrrhiza Glabra (Licorice) Root Extract, Sodium Hyaluronate, Cetyl Alcohol, Stearyl Alcohol, Citric Acid, Polygonum Cuspidatum Root Extract, Aloe Barbadensis Leaf Extract, Xanthan Gum, Camellia Sinensis Leaf Extract, Rosmarinus Officinalis (Rosemary) Leaf Extract, Chamomilla Recutita (Matricaria) Flower Extract, Bioflavonoids, Beta-Glucan, Brassica Oleracea Italica (Broccoli) Extract, *Limonene (essential oil component)